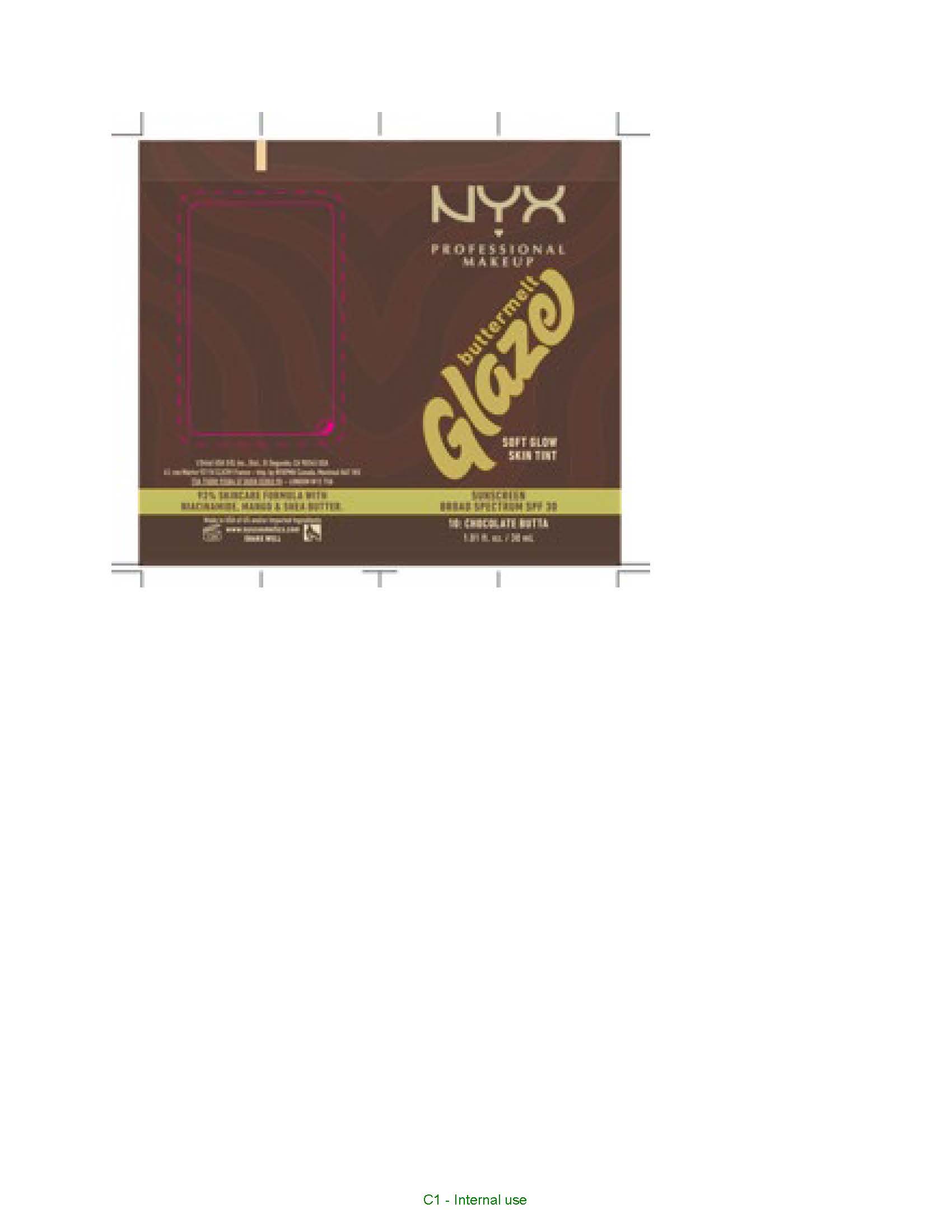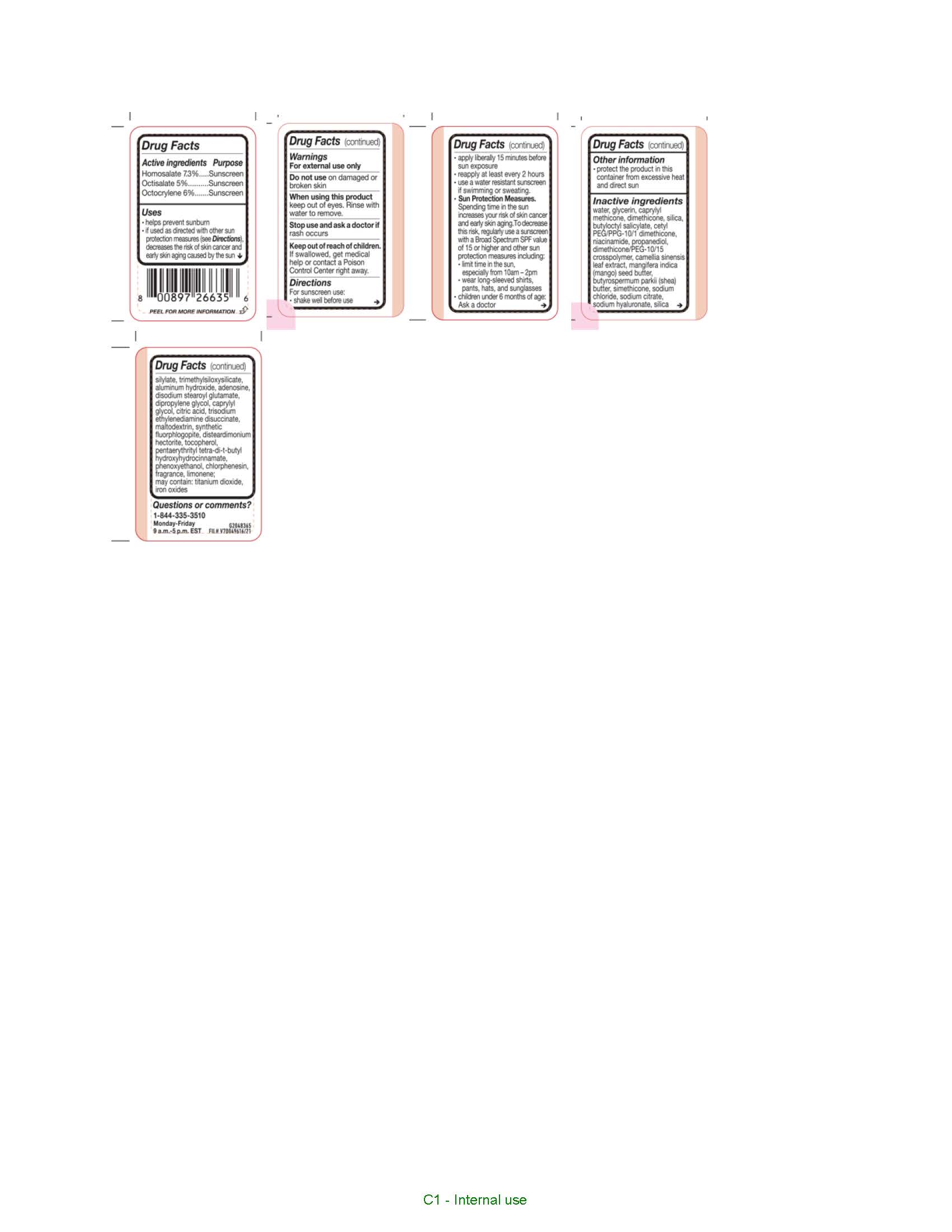 DRUG LABEL: NYX Professional Makeup Buttermelt Glaze SOFT GLOW SKIN TINT SUNSCREEN BROAD SPECTRUM SPF 30
NDC: 49967-356 | Form: CREAM
Manufacturer: L’Oreal USA Products Inc
Category: otc | Type: HUMAN OTC DRUG LABEL
Date: 20241223

ACTIVE INGREDIENTS: HOMOSALATE 73 mg/1 mL; OCTISALATE 50 mg/1 mL; OCTOCRYLENE 60 mg/1 mL
INACTIVE INGREDIENTS: WATER; GLYCERIN; CAPRYLYL METHICONE; DIMETHICONE; SILICA; BUTYLOCTYL SALICYLATE; NIACINAMIDE; PROPANEDIOL; DIMETHICONE/PEG-10/15 CROSSPOLYMER; CAMELLIA SINENSIS LEAF; MANGIFERA INDICA (MANGO) SEED BUTTER; BUTYROSPERMUM PARKII (SHEA) BUTTER; SODIUM CHLORIDE; SODIUM CITRATE; SODIUM HYALURONATE; TRIMETHYLSILOXYSILICATE (M/Q 0.6-0.8); ALUMINUM HYDROXIDE; ADENOSINE; DISODIUM STEAROYL GLUTAMATE; DIPROPYLENE GLYCOL; CAPRYLYL GLYCOL; CITRIC ACID; TRISODIUM ETHYLENEDIAMINE DISUCCINATE; MALTODEXTRIN; MAGNESIUM POTASSIUM ALUMINOSILICATE FLUORIDE; DISTEARDIMONIUM HECTORITE; TOCOPHEROL; PENTAERYTHRITYL TETRA-DI-T-BUTYL HYDROXYHYDROCINNAMATE; PHENOXYETHANOL; CHLORPHENESIN; LIMONENE, (+)-; TITANIUM DIOXIDE; IRON OXIDES

Drug Facts

Active ingredients

Homosalate 7.3%

Octisalate 5%

Octocrylene 6%

Purpose

Sunscreen

Uses

- helps prevent sunburn
- if used as directed with other sun protection measures (see Directions), decreases the risk of skin cancer and early skin aging caused by the sun

Warnings

For external use only

Do not use

on damaged or broken skin

When using this product

keep out of eyes. Rinse with water to remove.

Stop use and ask a doctor if

rash occurs

Keep out of reach of children.

If swallowed, get medical help or contact a Poison Control Center right away.

Directions

For sunscreen use:

- shake well before use
- apply liberally 15 minutes before sun exposure
- reapply at least every 2 hours
- use a water resistant sunscreen if swimming or sweating.
- Sun Protection Measures. Spending time in the sun increases your risk of skin cancer and early skin aging. To decrease this risk, regularly use a sunscreen with a Broad Spectrum SPF value of 15 or higher and other sun protection measures including:

o limit time in the sun, especially from 10am - 2pm

o wear long-sleeved shirts, pants, hats, and sunglasses

- children under 6 months of age: Ask a doctor

Other information

- protect the product in this container from excessive heat and direct sun

Inactive ingredients

water, glycerin, caprylyl methicone, dimethicone, silica, butyloctyl salicylate, cetyl PEG/PPG-10/1 dimethicone, niacinamide, propanediol, dimethicone/PEG-10/15 crosspolymer, camellia sinensis leaf extract, mangifera indica (mango) seed butter, butyrospermum parkii (shea) butter, simethicone, sodium chloride, sodium citrate, sodium hyaluronate, silica silylate, trimethylsiloxysilicate, aluminum hydroxide, adenosine, disodium stearoyl glutamate, dipropylene glycol, caprylyl glycol, citric acid, trisodium ethylenediamine disuccinate, maltodextrin, synthetic fluorphlogopite, disteardimonium hectorite, tocopherol, pentaerythrityl tetra-di-t-butyl hydroxyhydrocinnamate, phenoxyethanol, chlorphenesin, fragrance, limonene; may contain: titanium dioxide, iron oxides

Questions or comments?

1-844-335-3510

Monday-Friday

9 a.m.-5 p.m. EST